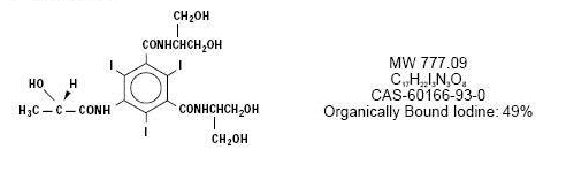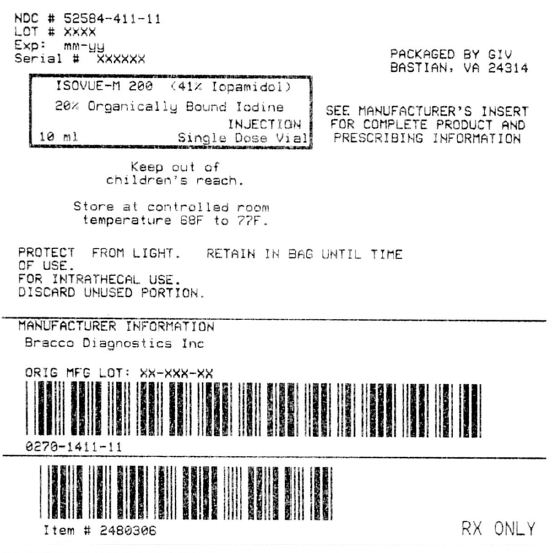 DRUG LABEL: ISOVUE-M 200
NDC: 52584-411 | Form: INJECTION, SOLUTION
Manufacturer: General Injectables & Vaccines, Inc.
Category: prescription | Type: HUMAN PRESCRIPTION DRUG LABEL
Date: 20170117

ACTIVE INGREDIENTS: Iopamidol 408 mg/1 mL
INACTIVE INGREDIENTS: Tromethamine; Edetate Calcium Disodium

ISOVUE-M 200

Description

Diagnostic

NONIONIC RADIOPAQUE CONTRAST MEDIA

For Intrathecal Administration in Neuroradiology

Including Myelography (Lumbar, Thoracic, Cervical, Total Columnar) Pediatric Myelography (Lumbar, Thoracic), and for Contrast Enhancement of Computed Tomographic (CECT) Cisternography and Ventriculography

ISOVUE-M (Iopamidol Injection) formulations are stable, aqueous, sterile, and nonprrogenic solutions for intrathecal administration. Each mL of ISOVUE-M 200 (lopamidol Injection 41%) provides 408 mg iopamidol with 1mg tromethamine and 0.26 mg edetate calcium disodium. The solution contains approximately 0.029 mg (0.001mEq) sodium and 200 mg organically bound iodine per mL. Each mL of ISOVUE-M 300 (lopamidol Injection 61%) provides 612 mg iopamidol with 1 mg tromethamine and 0.39 mg edetate calcium disodium. The solution contains approximately 0.043 mg (0.002 mEq) sodium and 300 mg organically bound iodine per mL. The pH of ISOVUE-M contrast media has been adjusted to 6.5-7.5 with hydrochloric acid and/or sodium hydroxide. Pertinent physicochemical data are noted below. ISOVUE-M (lopamidol Injection) is hypertonic as compared to plasma and cerbrospinal fluid (approximately 285 and 301 mOsm/kg water, respectively).

 | Iopamidol
Parameter | 41% | 61%
Concentration | 200 | 300
(mgl/mL)
Osmolality @ 37 degrees C | 413 | 616
(mOsm/kg water)
Visosity (cP) @ 37 degrees C | 2.0 | 4.7
@ 20 degrees C | 3.3 | 8.8
Specific Gravity @37 degrees C | 1.216 | 1.328

Iopamidol is designated chemically as (s)-N,N'-bis[2-hydroxy-1-(hydroxymethyl)-ethyl]-2, 4, 6,-triiodo-5-lactamidoisophthalamide. Structural formula:

Clinical Pharmacology

The pharmacokinetics of intravenously administered iopamidol in normal subjects conform to an open two-compartment model with first order elimination (a rapid alpha phase for drug distribution and a slow beta phase for drug elimination). The elimination serum or plasma half-life is approximately two hours; the half-life is not dose dependent. No significant metabolism, deiodination, or biotransformation occurs. Iopamidol is rapidly absorbed into the bloodstream from cerebrospinal fluid (CSF); following intrathecal administration, iopamidol apperrs in plasma within one hour and virtually all of the drug reaches the systemic circulation within 24 hours, Iopamidol is excreted mainly through the kidneys following intrthecal administration, and the drug is essentially undetectable in the plasma 48 hours later. In patients with impaired renal function, the elimination half-life is prolonged dependent upon the degree of impairment. In the absence of renal dysfunction, the cumulative urinary excretion for iopamidol, expressed as a percentage of administered intravenous dose is approximately 35 to 40 percent at 60 minutes, 80 to 90 percent at 8 hours, and 90 percent or more in the 72- to 96-hour period after admininstration. In normal subjects approximately 1 percent or less of the administered dose appears in cumulative 72- to 96-hour fecal specimens. Iopamidol displays little tendency to bind to serum or plasma proteins. No evidence of in vivo complement activation has been found in normal subjects. Animal studies indicate that iopamidol does not cross the blood-brain barrier to any significant extent following intravascular administration.

Indications and Usage

ISOVUE-M (Iopamidol Injection) is indicated for intrathecal administration in adult neuroradiology inculding myelography(lumbar, thoracic, cervical, total columnar), and for contrast enhancement of computed tomographic (CECT) cisternography and ventriculography. ISOVUE-M 200 (lopamidol Injection) is indicated for thoraco-lumbar myelography in children over the age of two years.

Contraindications

Intrathecal administration of corticosteroids with iopamidol is contraindicated. Because of overdosage considerations, immediate repeat myelography in the event of technical failure is contraindicated (see interval recommendation under DOSAGE AND ADMINISTRATION). Myelography should not be performed in the presence of significant local or systemic infection where bacteremia is likely.

Warnings

The need for myelographic examination should be carefully evaluated. Iopamidol should be administered with caution in patients with increased intrcranial pressure or suspicion of intracranial tumor, abscess or hematoma, those with a history of convulsive disorder, severe cardiovascular disease, chronic alcoholism, or multiple sclerosis, and elderly patients. Particular attention must be given to state of hydration, concentration of medium, dose, and technique used in these patients. Contrast media may promote sickling in individuals who are homozygous for sickle cell disease when injected intravenously or intra-arterially. Although ISOVUE-M is not injected intravascularly, measurable plasma levels are attained after intrathecal administration of iopamidol. If frankly bloody cerebrospinal fluid is observed, the possible benefits of a myelographic examination should be considered in terms of risk to the patient.

Patients on anticonvulsant medication should be maintained on this therapy.

Direct intracisternal or ventricular administration for standard radiography (without computerized tomographic enhancement) is not recommended. Inadvertent intracranial entry of a large or concentrated bolus of the contrast medium, which increase the risk of neurotoxicity, can be prevented by careful patient management. Also, effort should be directed to avoid rapid dispersion of the medium causing inadvertent rise to intracranial levels (e.g., by active patient movement). If such intracranial entry of the medium occurs, prophylactic anticonvulsant treatment with diazepam or barbiturates orally for 24 to 48 hours should be considered.

Use of medications that may lower the seizure thresnold (phenothiazine derivatives, including those used for their antihistaminic properties; tricyclic antidepressants; MAO inhibitors; CNS stimulants; analeptics; antipsychotic agents) should be carefully evaluated While the contributory role of such medications has not been established, some physicians have discontinued these agents at least 48 hours before and for at least 24 hours following intrathecal use.

Focal and generalized motor seizures have been reported after intrathecal use of water-soluble contrast agents including iopamidol. In several of those cases reported with iopamidol, higher than recommended doses were employed. Therfore avoid:

- Deviations from recommended neuroradiologic procedure or patient management.
- Use in patients with a history of epilepsy unless medically justified.
- Overdosage.
- Intracranial entry of a bolus or premature diffusion of a high concentration of the medium.
- Failure to maintain elvation of the head during the procedure, on the stretcher, and in bed.
- Excessive and particularly active patient movement or straining.

Precautions

General

Diagnostic procedures which involve the use of any radiopaque agent should be carried out under the direction of personnel with the prerequisite training and with a thorough knowledge of the particular procedure to be performed. Appropriate facilities should be available for coping with any complication of the procedure, as well as for emergency treatment of severe reaction to the contrast agent itself. After parenteral administration of a radiopaque agent, competent personnel and emergency facilities should be available for at least 30 to 60 minutes since sever delayed reactions may occur.

Preparatory dehydration is dangerous and may contribute to acute renal failure in patients with advanced vascular disease, diabetic patients, and in susceptible nondiabetic patients (often elderly with preexisting renal disease). Patients should be well hydrated prior to and following iopamidol administration.

Preparatory dehydration is dangerous and may contribute to acute renal failure in patients with advanced vascular disease, diabetic patients, and in susceptible nondiabetic patients (often elderly with preexisting renal disease). Patients should be well hydrated prior to following iopamidol administration.

The possibility of a reaction, including serious, life-threatening, fatal, anaphylactoid or cardiovascular reactions, should always be considered (see ADVERSE REACTIONS). Patients at increased risk include those with a history of a previous reaction to a contrast medium, patients with a know sensitivity to iodine per se, and patients with a know clinical hypersensitivity (bronchial asthma, hay fever, and food allergies). The occurrence of sever idiosyncratic reactions has prompted the use of several pretesting methods. However, pretesting cannot be relied upon to predict severe reactions and may itself be hazardous for the patient. It is suggested that a thorough medical history with emphasis on allergy and hypersensitivity, prior to the injection of any contrast medium, may be more accurate than pretesting in predicting potential adverse reactions. A positive history of allergies or hypersensitivity does not arbitrarily contraindicate the use of a contrast agent where a diagnostic procedure is thought essential, but caution should be exercised. Premedication with antihistamines or corticosteroids to avoid or minimize possible allergic reactions in such patients should be considered (see CONTRAINDICATIONS).

Reports indicate that such pretreatment does not prevent serious life-threatening reactions, but may reduce both their incidence and severity.

The possibility of inducing bacterial meningitis in patients during intrathecal procedures should always be considered. To avoid bacterial contamination during spinal puncture, a sterile field should be maintained at all times.

If nondisposable equipment is used, scrupulous care should be taken to prevent residual contamination with traces of cleansing agents.

Information for Patients

Patients receiving injectable radiopaque diagnostic agents should be instructed to:

1. Inform your physician if you are pregnant.

2. Inform your physician if you are diabetic or if you have multiple myeloma, pheochromocytoma, homozygous sickle cell disease, or known thyroid disorder.

3. Inform your physician if you are allergic to any drugs, food, or if you had any reactions to previous injections of substance used for x-ray procedures (see PRECAUTIONS-General).

4. Inform your physician about any other medications you are currently taking, including nonprescription drug, before you have this procedure.

Drug Interactions

Other drugs should not be admixed with iopamidol (see CONTRAINDICATIONS, and DOSAGE AND ADMINISTRATION, Drug Incompatibilities).

Drug/Laboratory Test Interactions

The results of PBI and radioactive iodine uptake studies, which depend on iodine estimations, will not accurately reflect thyroid function for up to 16 days following administration of iodinated contrast media. However, thyroid function tests not depending on iodine estimations, e.g., T3 resin uptake and total or free thyroxine (T4) assays are not affected. Any test which might be affected by contrast media should be performed prior to administration of the contrast medium.

Laboratory Test Findings

In vitro studies with animal blood showed that many radiopaque contrast agents, including iopamidol, produced a slight depression of plasma coagulation factors including prothrombin time, partial thromboplastin time, and fibrinogen, as well as a slight tendency to cause platelet and /or red blood cell aggregation.
Transitory changes may occur in red cell and leucocyte counts, serum calcium, serum creatinine, serum glutamic oxalacetic transaminase (SGOT), and uric acid in urine; transient albuminuria may occur.
These findings have not been associated with clinical manifestations.
Carcinogenesis, Mutagenesis, Impairment of Fertility
Long-term studies in animals have not been performed to evaluate carcinogenic potential. No evidence of genetic toxicity was obtained in vitro tests.
Pregnancy: Teratogenic Effects
Pregnancy Category B Reproduction studies have been performed in rats and rabbits at doses up to 2.7 and 1.4 times the maximum recommended human dose (1.48gl/kg in a 50kg individual). respectively, and have revealed no evidence of impaired fertility or harm to the fetus due to iopamidol. There are, however, no adequate and well-control studies in pregnant women. Because animal reproduction studies are not always predictive of human response, this drug should be used during pregnancy only id clearly needed.
Nursing MothersIt is not known whether this drug is excreted in human milk. Because many drugs are excreted in human milk, caution should be exercised when iopamidol is administered to a nursing woman.
Pediatric Use
See DOSAGE AND ADMINISTRATION section.

Adverse Reaction

The most frequently reported adverse reactions following intrathecal administration of iopamidol are headache, nausea, vomiting, and musculoskeletal pain. These reactions usually occur 1 to 10 hours after injection, almost all occurring within 24 hours. They are usually mild to moderate in degree, lasting for a few hours and usually disappearing within 24 hours. Rarely, headaches may be severe or persist for days. Headache is often accompanied by nausea and vomiting, and tends to be more frequent and persistent in patients not optimally hydrated. Backache, neck stiffness, numbness and paresthesias, leg or sciatic-type pain occurred less frequently, often in the form of a transient exacerbation of preexisting symptomatology. Transient alterations in vital signs may occur and their significance must be assessed on an individual basis.

The following table of incidence of reactions is based on clinical studies with ISOVUE-M (lopamidol Injection) in about 686 patients.

Adverse Reactions
 | Estimated Overall Incidence
System | Greater than 1% | less than or Equal to 1%
Body as a Whole | headache (16.4%) | pyrexia
 |  | muscle weakness
 |  | hot flashes
 |  | malaise
 |  | fatigue
 |  | weakness
Digestive | nausea (7.3%) | diarrhea
 | vomiting (3.6%) | heartburn
Musculoskeletal | back pain (2.2%) | leg cramps
 | leg pain (1.4%) | sciatica
 | neck pain (1.1%) | cervicobrachial irritation
 |  | meningeal irritation
 |  | radicular irritation
 |  | lumbosacral
 |  | other musculoskeletal
 |  | pain
 |  | involuntary movement
 |  | burning sensation
Cardiovascular | hypotension (1.1%) | tachycardia
 |  | hypertension
 |  | chest pain
Nervous | none | emotional stress
 |  | dizziness
 |  | paresthesia
 |  | confusion
 |  | hallucinations
 |  | lightheadedness
 |  | syncope
 |  | numbness
 |  | cold extremities
 |  | ataxia
 |  | irritability
Urogenital | none | urinary retention
Respiratory | none | dyspnea
Skin and Appendages | none | rash
Miscellaneous | none | injection site pain

Other adverse effects reported in clinical literature for iopamidol include facial neuralgia, tinnitus, and sweating.
Major motor seizures have been reported in the clinical literature and since market introduction in th eUnited States. Early onset of seizures (less than two hours) is indicative of early substantial intrcranial entry. Transitory EEG changes occur and usually take the form of slow wave activity.
While not observed in controlled clinical studies with ISOVUE-M (Iopamidol Injection), the following adverse reactions may occur because they have been reported with ISOVUE-M and other nonionic water soluble contrast agents: cardiovascular (arrhythmias); pulmonary (apnea); bacterial meningitis, and aseptic meningitis syndrome; allergy or idiosyncrasy (chills, pruritus, nasal congestion, Guillain_Barre syndrome); CNS irritation (psycho-organic syndrome : mild and transitory perceptual aberrations such as depersonalization, anxiety, deppression, hyperreflexia or areflexia, hypertonia or flaccidity, restlessness, tremor, echoacousia,echolalia, asterixis or dysphasia have occurred). Profound mental disturbances have rarely been reported (various forms and degrees of aphasia, mental confusion or disorientation); the onset is usually at 8 to 10 hours and lasts for about 24 hours without aftereffects. However, occasionally they have been manifest as apprehension, agitation or progressive withdrawal to the point of stupor or coma. In a few cases, these have been accompanied by transitory hearing loss or other auditory symptoms and visual disturbances (believed subjective or delusional). Persistent cortical loss of vision in association with convulsions, and ventricular block have been reported. Rarely, persistent though transitory weakness in the leg or ocular muscles has been reported. Peripheral neuropathies have been rare and transitory. They include sensory and/or motor or nerve root disturbances, myelitis, persistent leg muscle pain or weakness, or sixth nerve palsy, or cauda equina syndrome. Muscle cramps, fasciculation or myoclonia, spinal convulsion, paralysis, or spasticity are unusual.
General Adverse Reactions To Contrast MediaReactions known to occur with parenteral administration of iodinated ionic contrast agents (see the listing below) are possible with any nonionic agent. Approximately 95 percent of adverse reactions accompanying the use of other water-soluble intrvascularly administered contrast agents are mild to moderate in degree. However, life-threatening reactions and fatalities, mostly of cardiovascular origin, have occurred. Reported incidences of death from the administration of other iodinated contrast media range from 6.6 per 1 million (0.00066 percent) to 1 in 10,000 patients (0.01 percent). Most deaths occur during injection or 5 to 10 minutes later, the main feature being cardiac arrest with cardiovascular disease as the main aggravating factor. Isolated reports of hypotensive collapse and shock are found in the literature. The incidence of shock is estimated to be 1 out of 20,000 (0.005 percent) patients.
Adverse reactions to injectable contrast media fall into two categories: chemotoxic reactions and idiosyncratic reactions. Chemotoxic reactions result from the physicochemical properties of the contrast medium, the dose, and the speed of injection. All hemodynamic disturbances and injuries to organs or vessels perfused by the contrast medium are included in this category. During intrathecal use, there is a lower incidence of electroencephalographic changes as well as neurotoxicity by virtue of the intrinsic properties of the iopamidol molecule.
Idiosyncratic reactions include all other reactions. They occur more frequently in patients 20 to 40 years old. Idiosyncratic reactions may or may not be dependent on the amount of drug injected, the speed of injection, the mode of injection, and the radiographic procedure. Idiosyncratic reactions are subdivided into minor, intermediate, and severe. The minor reactions are self-limited and of short duration; the severe reactions are life-threatening and treatment is urgent and mandatory.
The reported incidence of adverse reactions to contrast media in patients with a history of allergy is twice that for the general population. Patients with a history of previous reactions to a contrast medium are three times more susceptible than other patients. However, sensitivity to contrast media does not appear to increase with repeated examinations. Most adverse reactions to intravascular contrast agents appear within one to three minutes after the start of injection, but delayed reactions may occur (see PRECAUTIONS-GENERAL).
Because measurable plasma levels are attained following the intrathecal administration of lopamidol, adverse reactions reported with the use of intravascular contrast agents are theoretically possible. These include:
Cardiovascular: vasodilation (feeling of warmth), cerebral hematomas, hemodynamic disturbances, sinus brady cardia, transient electrocardiographic abnormalities, ventricular fibrillation, pentechiae.
Digestive: nausea, vomiting, severe unilateral or bilateral swelling of the parotid and submaxillary glands.
Nervous: paresthesia, dizziness, convulsions, paralysis, coma.
Respiratory: increased cough, asthma, dyspnea, laryngeal edema, pulmonary edema, bronchospasm, rhinitis.
Skin and Appendages: injection site pain usually due to extravasation and/or erythematous swelling, skin necrosis, urticaria.
Urogenital: osmotic nephrosis of proximal tubular cells, renal failure, pain.
Special Senses: perversion of taste; bilateral ocular irritation; lacrimation; itching; conjunctival chemosis, infection, and conjunctivitis.
The following reactions may also occur: neutropenia, thrombophlebitis, flushing, pallor, weakness, severe retching and chocking, wheezing, cramps, tremors, and sneezing.

Overdosage

A dose of 3000 mgl in adults and 2400 mgl in children is sufficient for most myelographic procedures. Doses above these levels may result in an increased frequency and severity of adverse reactions including seizures. However, in myelography, even use of a recommended dose can produce mental aberrations tantamount to overdosage, if incorrect management of the patient during or immediately following the procedure permits inadvertent early intracranial entry of a large portion of the medium.
Treatment of an overdose of an injectiable radiopaque contrast medium is directed toward the support of all vital functions, and prompt institution of symptomatic therapy.

Dosage and Administration

In adults a solution that is approximately isotonic (ISOVUE-M 200) is recommended for examination of the lumbar region. For movement of the contrast medium to distant target areas the more concentrated ISOVUE-M 300 preparation should be used to compensate for dilution of ISOVUE-M (lopamidol Injection) with cerebrospinal fluid.
The usual recommended adult dose range for iopamidol is 2000-3000 mg iodine. Iopamidol formulated to contain more than 300 mgl/ml should not be used intrathecally in adults. The minimum dose needed to perform a procedure should always be used.

In pediatric patients, a solution that is approximately isotonic (ISOVUE-M 200) is recommended for all intrathecal procedures. In children, loss of contrast due to mixing on movement of the medium is less apt to occur because of their shorter spinal cord.

The usual recommended pediatric dose range for iopamidol is 1400-2400 mg iodine. Iopamidol formulated to contain more than 200 mgl/ml should not be used. See pediatric dosage table for recommended dosage.
Anesthesia is not necessary. However, young children may require general anesthesia for technical reasons. Premedication with sedatives or tranquillizers is usually not needed. In patients with a history of seizure activity who are on anticonvulsant therapy, premedication with barbiturates or phenytoin should be considered.
Lumbar puncture is usually made between L3 and L4; if pathology is suspected at this level, the interspace immediately above or below may be selected. A lateral cervical puncture may also be used.
Rate of Injection: To avoid excessive mixing with cerebrospinal fluid and consequent loss of contrast as well as premature cephalad dispersion, injection must be made slowly over one to two minutes; the needle may
then be removed.
An interval of at least 48 hours should be allowed before repeat examination; however, whenever possible five to seven days is
recommended.
As with all radiopaque contrast agents, only the lowest dose of ISOVUE-M necessary to obtain adequate visualization should be used. A lower dose reduces the possibility of an adverse reaction. Most procedures do not require use of either a maximum dose or the highest available concentration of ISOVUE-M; the combination of dose and ISOVUE-M concentration to be used should be carefully individualized, and factors such as age, body size, anticipated pathology and degree and extent of opacification required, structure(s) or area to be examined, disease processes affecting the patient, and equipment and technique to be employed should be considered. Following are the usual recommended pediatric and adult doses of ISOVUE-M.
The pediatric doses listed below, intended as a guideline, are based on age rather than weight because the brain and CSF capacity is independent of weight. Variations will depend on such factors as height, suspected pathology, the patient's condition, technique used, etc. (e.g. CT or standard radiology or movement of the contrast media directed distal to the sit of injection).

Pediatric Dosage Table ISOVUE-M 200 (200mgl/mL)
 |  | Usual
 | Age | Recommended
Procedure | Years | Dose (mL)
Lumbar, thoracic myelogram | 2-7 | 7-9
 | 8-12 | 8-11
 | 13-18 | 10-12

Adult Dosage Table
 |  | Usual
 | Concentration | Recommended
 | of Solution | Dose
 | (mgl/mL) | (mL)
Lumbar myelogram | 200 | 10 to 15
Thoracic myelogram | 200 | 10 to 15
Cervical myelogram | 200 | 10 to 15
(via lumbar injection) | 300 | 10
Cervical myelogram | 200 | 10
(via lateral cervical injection)
Total columnar myelography | 300 | 10
CT cisternography | 200 | 4 to 6
(via lumbar injection)

Following subarachnoid injection, conventional radiography will continue to provide good diagnostic contrast for at lease 30 minutes. At about one hour, diagnostic degree of contrast will not usually be available. However, suffiicient contrast for CT myelography will be available for several hours. CT myelography following conventional myelography should be deferred for at least four hours to reduce the degree of contrast. Aspiration of iopamidol is unnecessary following intrathecal administration (see CLINICAL PHARMACOLOGY).
It is desirable that solutions of radio paque diagnostic agents for intrathecal use be at body temperature when injected. In the even that crystallization of the medium has occurred, place the vial in hot (60 degree to 100 degree C) water for about five minutes, then shake gently to obtain a clear solution. Cool to body temperature before use.
Discard vial without use if solids persist.
Withdrawal of contrast agents from their containers should be accomplished under aseptic conditions with sterile syringes. Spinal puncture must always be performed under sterile conditions.
Parenteral drug products should be inspected visually for particulate matter and discolorationprior to administration, whenever solution and container permit. Iopamidol solutions should be used only if clear and within the normal colorless to pale yellow range.
Patients should be well hydrated prior to and following ISOVUE-M (Iopamidol Injection) administration.
Suggestions for Usual Patient Management
Preprocedure
* See WARNINGS regarding discontinuation of neuroleptic agents
* Maintain normal diet up to 2 hours before procedure
* Ensure hydration-fluids up to time of procedure
During Procedure
* Use minimum dose and concentration required for satisfactory contrast.
* Inject slowly over 1 to 2 minutes to avoid excessive mixing.
* Abrupt or active patient movement causes excessive mixing with CSF.
* Instruct patient to remain passive. Move patient slowly and only as necessary.
* To maintain as a bolus, move medium to distal area very slowly under fluoroscopic control.
* In all positioning techniques keep the patient's head elevated above highest level of spine.
* Do not lower head of table more than 15 degrees during thoraco-cervical procedures.
* In patients with excessive lordosis, consider lateral position for injection and movement of the medium cephalad.
* Avoid intracranial entry of a bolus.
* Avoid early and high cephalad dispersion of the medium.
* At completion of direct cervical or lumbo-cervical procedures, raise head of table steeply (45 degrees) for about 2 minutes to restore medium to lower levels.
Post procedure
* Raise head of stretcher to at lease 30 degrees before moving patient onto it.
* Movement onto stretcher, and off the stretcher to bed, should be done slowly with patient completely passive, maintaining head up position.
* Before moving patient onto bed, raise head of be 30 degree to 45 degree and maintain the patient in this position under close observation for 12 to 24 hours.
* Advise patient to remain still in bed, in head up position for the first 24 hours.
* Obtain visitors cooperation in keeping the patient quiet and in head up position, especially in first few hours.
* Encourage oral fluids and diet as tolerated.
* Antinauseants of the phenothiazine class should not be administered to treat the postprocedural nausea or vomiting (see WARNINGS). Since persistent nausea and vomiting may result in dehydration, prompt consideration of volume replacement by intravenous fluids is recommended.
Drug Incompatibilities
Many radiopaque contrast agents are incompatible in vitro with some antihistamines and many other drugs; therefore, no other pharmaceuticals should be admixed with contrast agents.

How Supplied

ISOVUE-M 200 (Iopamidol Injection 41%)

Ten 10mL single dose vials (NDC 0270-1411-11)

Ten 20mL single dose vials (NDC 0270-1411-25)

ISOVUE-M 300 (Iopamidol Injection 61%)

Ten 15mL single dose vials (NDC 270-1412-15)

Storage

Store at 20-25 degrees C (68-77 degrees F). [See USP]. Protect from Light
RX ONLY
Manufactured for
Bracco Diagnostics Inc.
Princeton, NJ 08543
by Patheon Italia S.p.A.
03013 Ferentino (Italy)
Revised October 2005
255032